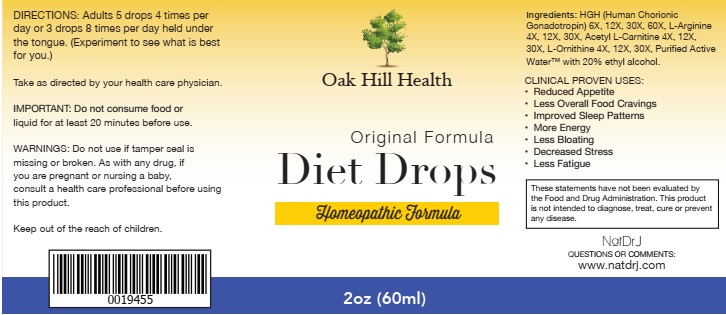 DRUG LABEL: Diet Drops
NDC: 71559-306 | Form: LIQUID
Manufacturer: NaturoDRJ Enterprises
Category: homeopathic | Type: HUMAN PRESCRIPTION DRUG LABEL
Date: 20190116

ACTIVE INGREDIENTS: CHORIONIC GONADOTROPIN 6 [hp_X]/60 mL; ARGININE 4 [hp_X]/60 mL; ACETYLCARNITINE 4 [hp_X]/60 mL; ORNITHINE 4 [hp_X]/60 mL
INACTIVE INGREDIENTS: WATER; ALCOHOL

Diet Drops

ACTIVE INGREDIENT

Ingredients: HGH (Human Chorionic Gonadotropin) 6X, 12X, 30X, 60X, L-Arginine 4X, 12X, 30X, Acetyl L-Carnitine 4X, 12X, 30X, L-Ornithine 4X, 12X, 30X, Purified Active Water™ with 20% ethyl alcohol.

These statements have not been evaluated by the Food and Drug Administration. This product is not intended to diagnose, treat, cure or prevent any disease.

INDICATIONS AND USAGE

CLINICAL PROVEN USES:

• Reduced Appetite

• Less Overall Food Cravings

• Improved Sleep Patterns

• More Energy

• Less Bloating

• Decreased Stress

• Less Fatigue

WARNINGS

WARNINGS: Do not use if tamper seal is missing or broken. As with any drug, if you are pregnant or nursing a baby, consult a health care professional before using this product.

Keep out of reach of children.

Keep out of reach of children.

DOSAGE AND ADMINISTRATION

DIRECTIONS: Adults 5 drops 4 times per day or 3 drops 8 times per day held under the tongue. (Experiment to see what is best for you.)

Take as directed by your health care physician.

OTHER SAFETY INFORMATION

IMPORTANT: Do not consume food or liquid for at least 20 minutes before use.

INACTIVE INGREDIENT

Purified Active Water™ with 20% ethyl alcohol.

QUESTIONS

NatDR J

QUESTIONS OR COMMENTS:

www.natdrj.com

PACKAGE LABEL

Oak Hill Health

Original Formula

Diet Drops

Homeopathic Formula

2oz (60ml)

PURPOSE

CLINICAL PROVEN USES:

• Reduced Appetite

• Less Overall Food Cravings

• Improved Sleep Patterns

• More Energy

• Less Bloating

• Decreased Stress

• Less Fatigue